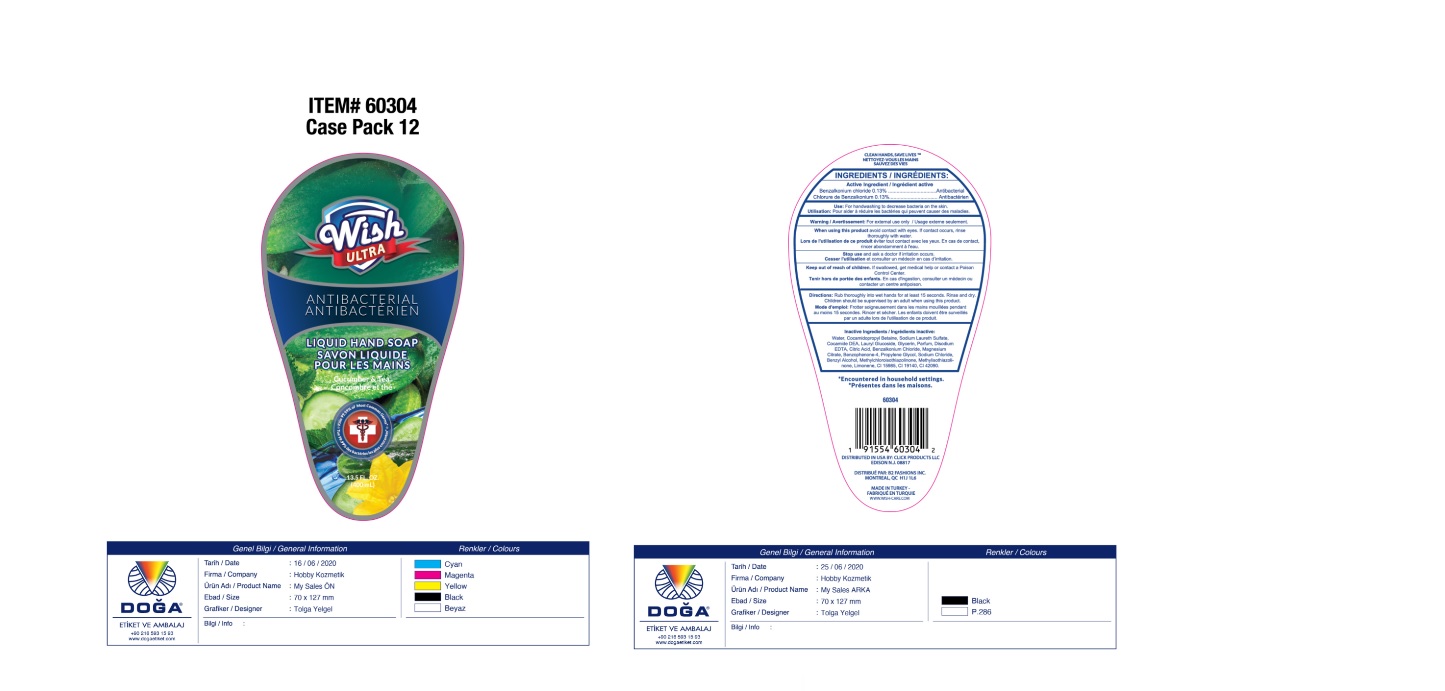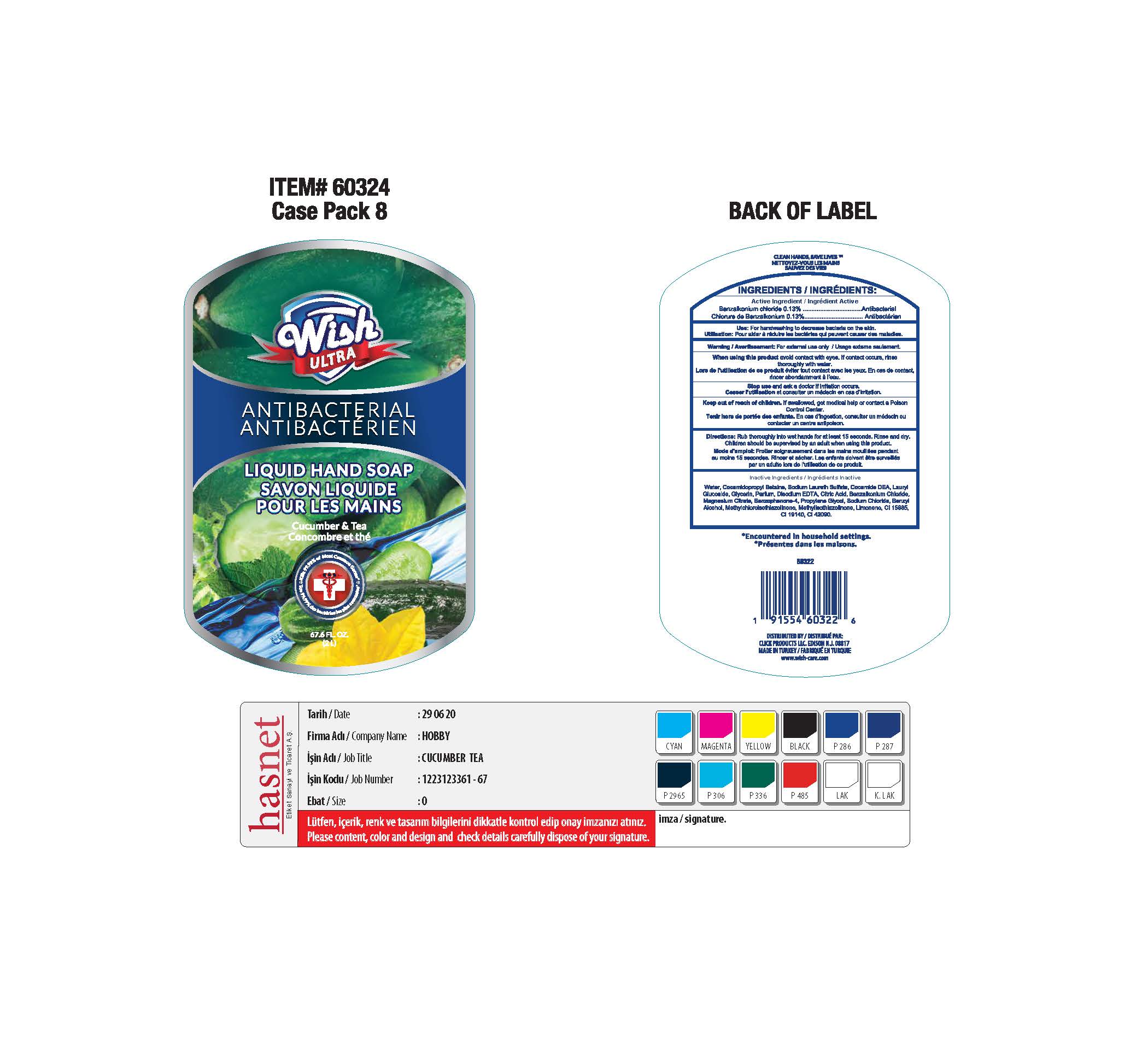 DRUG LABEL: ANTIBACTERIAL HANDWASH
NDC: 71611-068 | Form: LIQUID
Manufacturer: Click Products LLC
Category: otc | Type: HUMAN OTC DRUG LABEL
Date: 20200912

ACTIVE INGREDIENTS: BENZALKONIUM CHLORIDE 0.13 g/100 mL
INACTIVE INGREDIENTS: FD&C YELLOW NO. 5; PROPYLENE GLYCOL; LIMONENE, (+)-; METHYLCHLOROISOTHIAZOLINONE; METHYLISOTHIAZOLINONE; CITRIC ACID MONOHYDRATE; SODIUM CHLORIDE; WATER; SODIUM LAURETH-3 SULFATE; COCAMIDOPROPYL BETAINE; COCO DIETHANOLAMIDE; MAGNESIUM CITRATE; GLYCERIN; EDETATE DISODIUM ANHYDROUS; LAURYL GLUCOSIDE; SULISOBENZONE; FD&C BLUE NO. 1; FD&C YELLOW NO. 6; BENZYL ALCOHOL

Wish ULTRA ANTIBACTERIAL LIQUID HAND SOAP: cucumber & tea

Active Ingredient

Benzalkonium Chloride 0.13%

Purpose

Antibacterial

USES

- For Handwashing to decrease bacteria on the skin

WARNING

For external use only.

WHEN USING

- avoid contact with eyes.
- If contact occurs, rinse thoroughly with water.

Stop use and ask a doctor if

- If irritation occurs.

KEEP OUT OF REACH OF CHILDREN.

If swallowed, get medical help or contact a Poison Control Center immediately.

DIRECTIONS

- Rub thoroughly into wet hands for at least 15 seconds.
- Rinse and dry children should be supervised by an adult when using this product.

Inactive Ingredients:

Water（Aqua),Cocamidopropyl Betaine,Sodium Chloride,Fragrance, Citric Acid,Methylchloroisothiazolinone,Methylisothiazolinone, Sodium Laureth Sulfate , Cocamide DEA,Benzophenone-4,Parfum,Limonene,CI 15985,CI19140,Lauryl Glucoside.,CI 42090